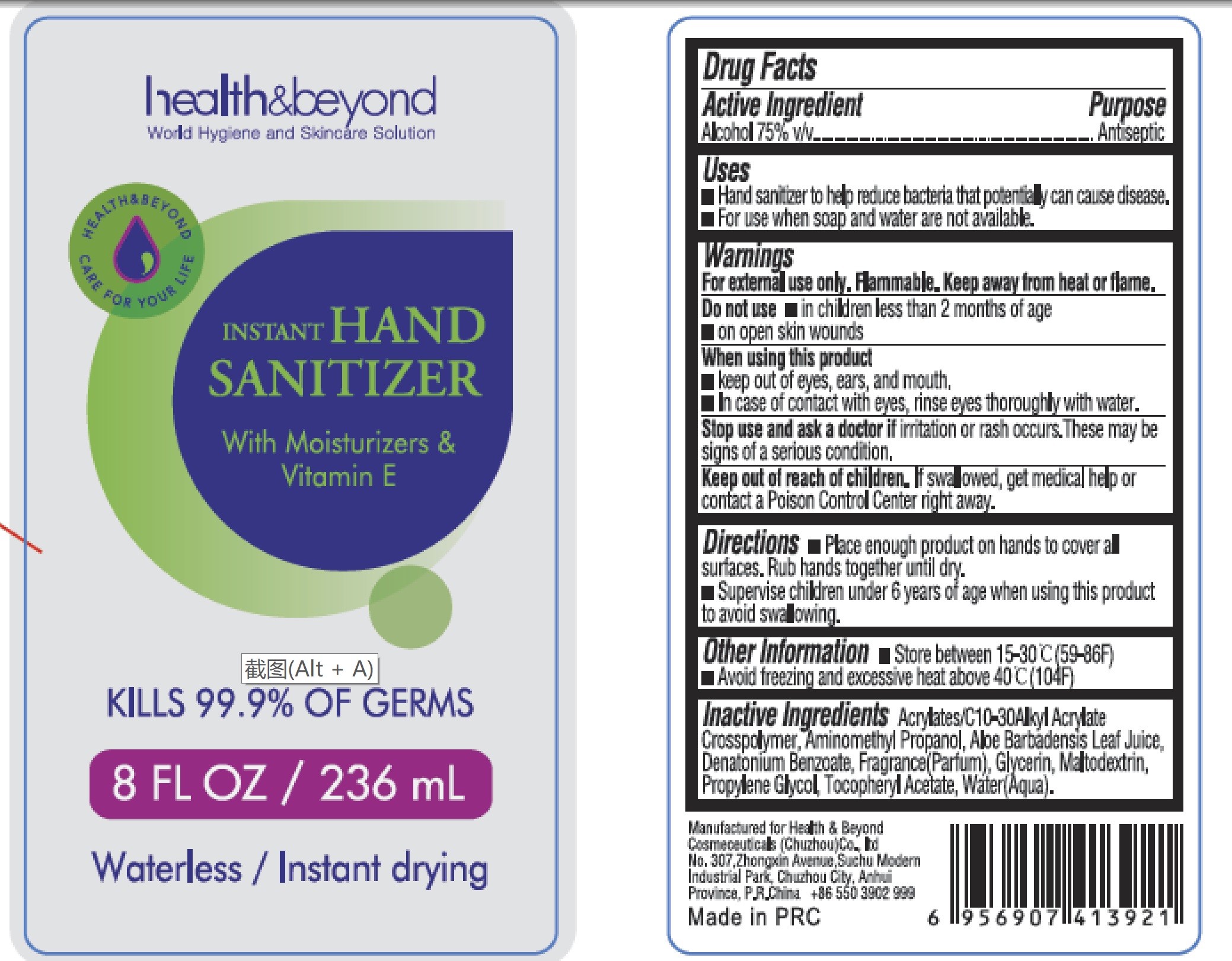 DRUG LABEL: INSTANT HAND SANITIZER
NDC: 81766-008 | Form: GEL
Manufacturer: Health & Beyond Cosmeceuticals (Chuzhou) Co., Ltd
Category: otc | Type: HUMAN OTC DRUG LABEL
Date: 20210404

ACTIVE INGREDIENTS: ALCOHOL 75 mL/100 mL
INACTIVE INGREDIENTS: MALTODEXTRIN; .ALPHA.-TOCOPHEROL ACETATE; WATER; DENATONIUM BENZOATE; CARBOMER COPOLYMER TYPE A (ALLYL PENTAERYTHRITOL CROSSLINKED); ALOE VERA LEAF; AMINOMETHYLPROPANOL; GLYCERIN; PROPYLENE GLYCOL

health & beyond
INSTANT HAND SANITIZER
8oz

Active Ingredient

Alcohol 75% v/v

Purpose

Antiseptic

Uses

- Hand sanitizer to help reduce bacteria that potentially can cause disease.
- For use when soap and water are not available.

Warnings

For external use only. Flammable. Keep away from heat or flame.

Do not use

- in children less than 2 months of age
- on open skin wounds

When using this product

- keep out of eyes, ears, and mouth.
- In case of contact with eyes, rinse eyes thoroughly with water.

Stop use and ask a doctor if

irritation or rash occurs. These may be signs of a serious condition.

Keep out of reach of children

If swallowed, get medical help or contact a Poison Control Center right away.

Directions

- Place enough product on hands to cover all surfaces. Rub hands together until dry.
- Supervise children under 6 years of age when using this product to avoid swallowing.

Other Information

- Store between 15-30℃ (59-86F°)
- Avoid freezing and excessive heat above 40℃(104°F)

Inactive Ingredients

Acrylates/C10-30Alkyl Acrylate Crosspolymer, Aminomethyl Propanol, Aloe Barbadensis Leaf Juice, Denatonium Benzoate, Fragrance(Parfum), Glycerin, Maltodextrin, Propylene Glycol, Tocopheryl Acetate, Water(Aqua).